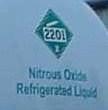 DRUG LABEL: Nitrous Oxide
NDC: 72343-001 | Form: GAS
Manufacturer: Nitrous Oxide of Canada
Category: prescription | Type: HUMAN PRESCRIPTION DRUG LABEL
Date: 20251111

ACTIVE INGREDIENTS: NITROUS OXIDE 900 mL/1 L

Nitrous Oxide

PACKAGE LABEL

Airgas

2201

Nitrous Oxide

Refrigerated Liquid